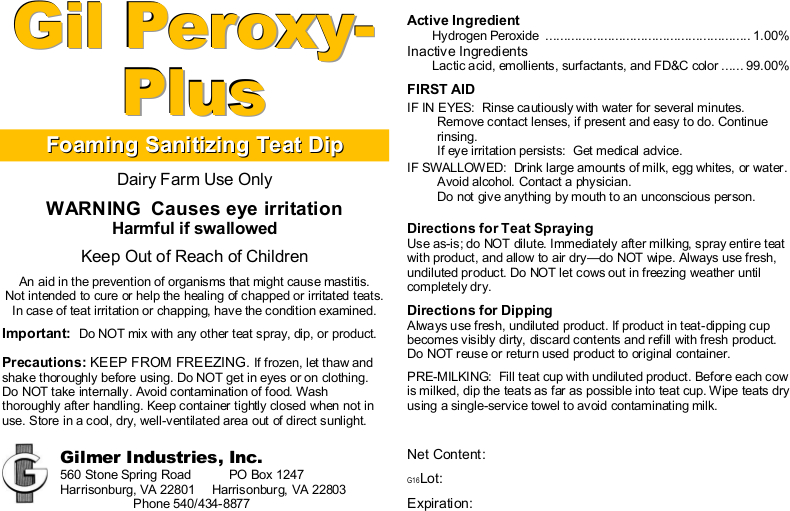 DRUG LABEL: Gil Peroxy-Plus
NDC: 54420-015 | Form: LIQUID
Manufacturer: Gilmer Industries, Inc.
Category: animal | Type: OTC ANIMAL DRUG LABEL
Date: 20160811

ACTIVE INGREDIENTS: HYDROGEN PEROXIDE 10000 mg/1 L

Gil Peroxy-Plus

PURPOSE

Foaming Sanitizing Teat Dip

Dairy Farm Use Only

WARNING Causes eye irritation Harmful if swallowed

Keep Out of Reach of Children

An aid in the prevention of organisms that might cause mastitis.

Not intended to cure or help the healing of chapped or irritated teats.

In case of teat irritation or chapping, have the condition examined.

Important: Do NOT mix with any other teat spray, dip, or product.

Precautions: KEEP FROM FREEZING. If frozen, let thaw and shake thoroughly before using. Do NOT get in eyes or on clothing. Do NOT take internally. Do NOT allow to contaminate food. Wash thoroughly after handling. Keep container tightly closed when not in use. Store in a cool, dry, well-ventilated area out of direct sunlight.

Active Ingredient

Hydrogen Peroxide ......................................................... 1.00%

Inactive Ingredients

Lactic acid, emollients, surfactants, and FD&C color.... 99.00%

USER SAFETY WARNINGS

FIRST AID

IF IN EYES: Rinse cautiously with water for several minutes. Remove contact lenses if present and easy to do. Continue rinsing.

If eye irritation persists: Get medical advice.

IF SWALLOWED: Drink large amounts of milk, egg whites, or water. Avoid alcohol. Contact a physician. Do not give anything by mouth to an unconscious person.

DOSAGE AND ADMINISTRATION

Directions for Teat Spraying

Use as-is; do NOT dilute. Immediately after milking, spray entire teat with product, and allow to air dry—do NOT wipe.
Do NOT let cows out in freezing weather until completely dry.

Directions for Dipping

Always use fresh, undiluted product. If product in teat-dipping cup becomes visibly dirty, discard contents and refill with fresh product.
Do NOT reuse or return used product to original container.
PRE-MILKING: Fill teat cup with undiluted product. Before each cow is milked, dip the teats as far as possible into teat cup. Wipe teats dry using a single-service towel to avoid contaminating milk.